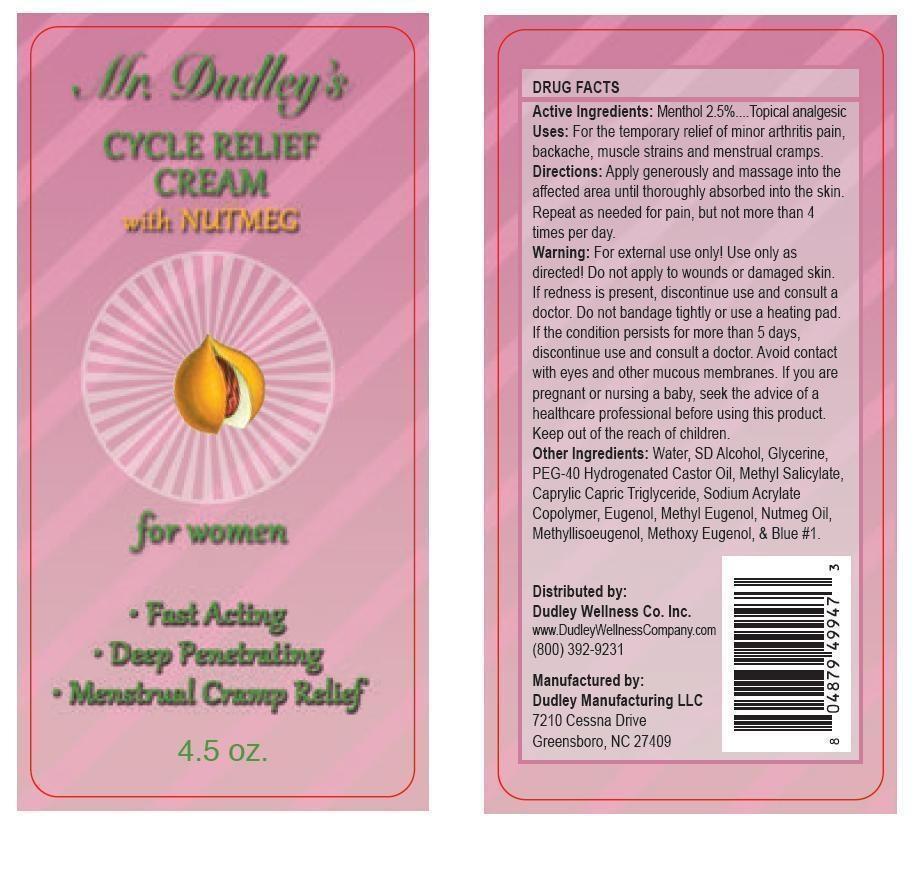 DRUG LABEL: Mr Dudleys Topical Cycle Relief with Nutmeg
NDC: 58484-200 | Form: CREAM
Manufacturer: Dudley Wellness Company Inc
Category: otc | Type: HUMAN OTC DRUG LABEL
Date: 20131024

ACTIVE INGREDIENTS: MENTHOL 2.5 g/100 g
INACTIVE INGREDIENTS: Methyl Salicylate; Water; ALCOHOL; GLYCERIN; POLYOXYL 40 HYDROGENATED CASTOR OIL; MEDIUM-CHAIN TRIGLYCERIDES; ACRYLAMIDE; EUGENOL; METHYL EUGENOL; NUTMEG OIL; METHYL ISOEUGENOL; FD&C BLUE NO. 1

Drug Fact

Active Ingredient

Menthol 2.5%

Purpose

Temporary relief of minor arthritis pain, backache, muscle strains, sprains, and mesntrual cramps.

Indications and Usage

Temporary relief of minor arthritis pain, backache, muscle strains, sprains, and mesntrual cramps.

Apply generously and massage into the affected area until throughly absorbed into the skin,repeat as and when needed for pain but not more than 4 times a day.

Warnings

Keep out of reach of children.

For esternal use only, use only as directed.

Donot apply to wound or broken skin.

If redness present discontinue and consult a doctor.

Do not bandage tightly or use a heating pad.

If the condition persists for more than 5 days, discontinue use and consult a doctor.

Avoid contact with eyes and other mucous membranes.

If you are pregnant or nursing a baby, seek the advice of a healthcare professional before using this product.

Dosage and administration.

Apply generously and massage into the affected area until throughly absorbed into the skin,repeat as and when needed for pain but not more than 4 times a day.

Inactive ingredient.

Water

SD Alcohol

Glycerine

PEG-440 Hydrogenated Castor Oil

Methyl Salicylate

Caprylic Capric Triglyceride

Sodium Acrylate Copolymer

Eugenol

Methyl Eugenol

Nutmeg Oil

Methyllisoeugenol

Methoxy Eugenol

Blue # 1